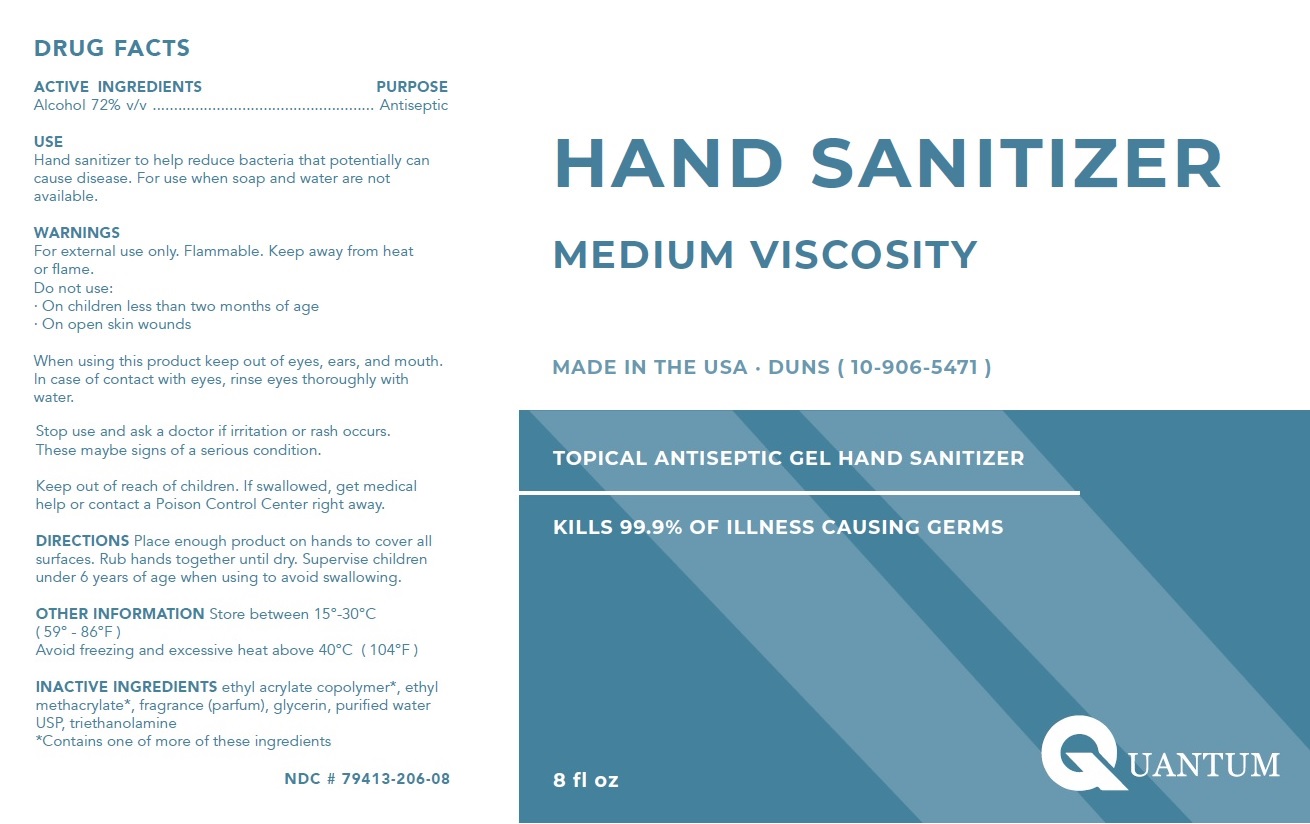 DRUG LABEL: Quantum Medium Viscosity Gel Hand Sanitizer
NDC: 79413-206 | Form: GEL
Manufacturer: Quantum Valve And Oilfield Solutions, Llc
Category: otc | Type: HUMAN OTC DRUG LABEL
Date: 20200904

ACTIVE INGREDIENTS: ALCOHOL 72 mL/100 mL
INACTIVE INGREDIENTS: ETHYL ACRYLATE; ETHYL METHACRYLATE; GLYCERIN; WATER; TROLAMINE

QUANTUM HAND SANITIZER MEDIUM VISCOSITY

ACTIVE INGREDIENTS

Alcohol 72% v/v

PURPOSE

Antiseptic

USE

Hand sanitizer to help reduce bacteria that potentially can cause disease. For use when soap and water are not available.

WARNINGS

For external use only. Flammable. Keep away from heat or flame.
Do not use:
· On children less than two months of age
· On open skin wounds
When using this product keep out of eyes, ears, and mouth. In case of contact with eyes, rinse eyes thoroughly with water.
Stop use and ask a doctor if irritation or rash occurs. These maybe signs of a serious condition.

Keep out of reach of children. If swallowed, get medical help or contact a Poison Control Center right away.

DOSAGE AND ADMINISTRATION

DIRECTIONS Place enough product on hands to cover all surfaces. Rub hands together until dry. Supervise children under 6 years of age when using to avoid swallowing.

OTHER INFORMATION Store between 15°-30°C (59° - 86°F)
Avoid freezing and excessive heat above 40°C (104°F)

INACTIVE INGREDIENT

INACTIVE INGREDIENTS ethyl acrylate copolymer*, ethyl methacrylate*, fragrance (parfum), glycerin, purified water USP, triethanolamine

*Contains one of more of these ingredients

MADE IN THE USA · DUNS (10-906-5471)

TOPICAL ANTISEPTIC GEL HAND SANITIZER
KILLS 99.9% OF ILLNESS CAUSING GERMS